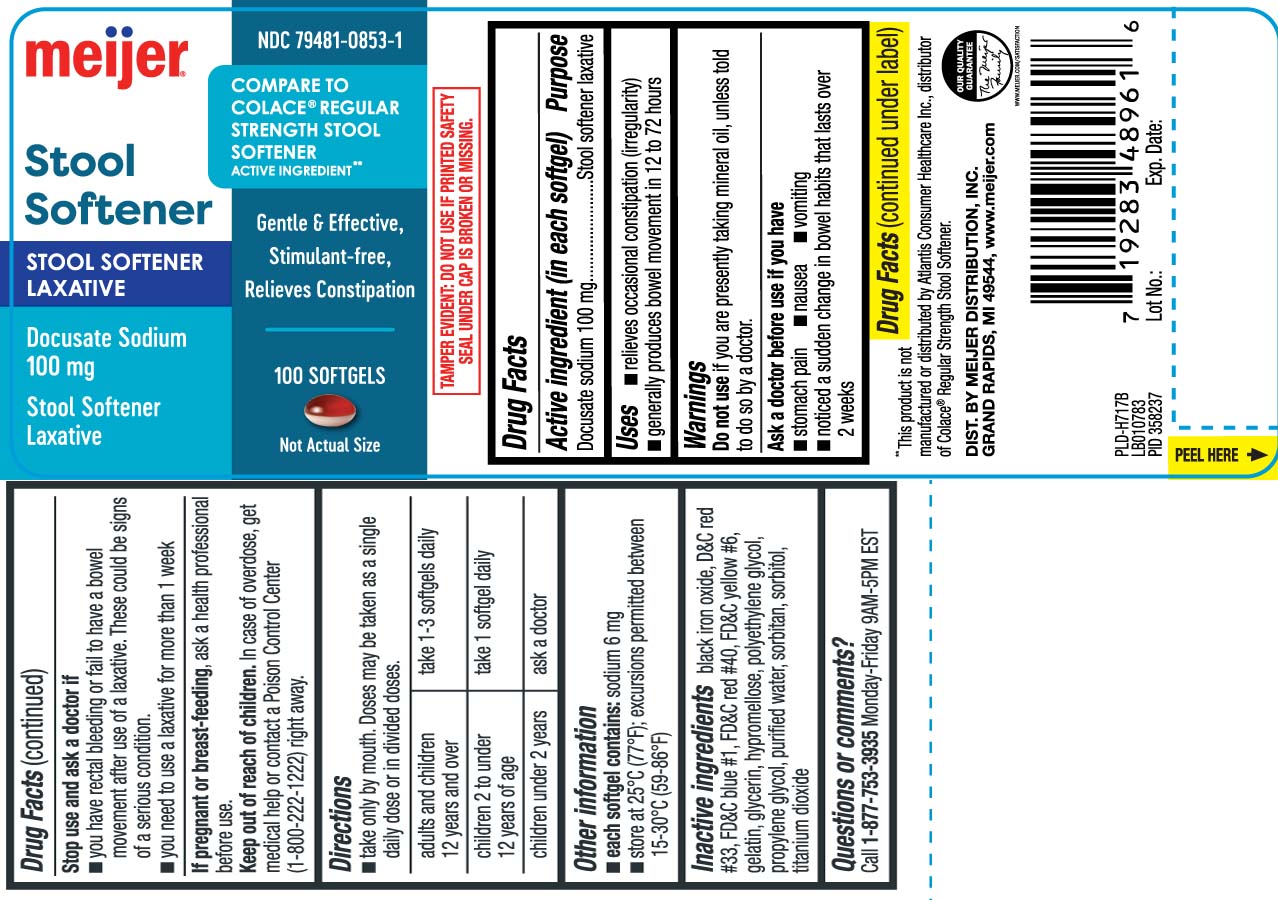 DRUG LABEL: Stool Softener Laxative
NDC: 79481-0853 | Form: CAPSULE, LIQUID FILLED
Manufacturer: Meijer Distribution Inc.
Category: otc | Type: HUMAN OTC DRUG LABEL
Date: 20260128

ACTIVE INGREDIENTS: DOCUSATE SODIUM 100 mg/1 1
INACTIVE INGREDIENTS: FD&C BLUE NO. 1; FD&C RED NO. 40; FD&C YELLOW NO. 6; GELATIN; GLYCERIN; POLYETHYLENE GLYCOL, UNSPECIFIED; PROPYLENE GLYCOL; WATER; SORBITAN; SORBITOL; TITANIUM DIOXIDE; D&C RED NO. 33; FERROSOFERRIC OXIDE

Drug Facts

Active Ingredient (in each softgel)

Docusate Sodium 100 mg

Purpose

Stool softener laxative

Uses

- relieves occasional constipation (irregularity)
- generally produces bowel movement in12 to 72 hours

Warnings

Do not use

if you are presently taking mineral oil, unless told so by a doctor.

Ask a doctor before use if you have

- stomach pain
- nausea
- vomiting
- noticed a sudden change in bowel habits that lasts over 2 weeks

Stop use and ask a doctor if

- you have rectal bleeding or fail to have a bowel movement after use of a laxative. These could be signs of a serious condition.
- you need to use a laxative for more than 1 week

If pregnant or breast-feeding,

ask a health care professional before use.

Keep out of reach of children.

In case of overdose, get medical help or contact a Poison Control Center (1-800-222-1222) right away.

Directions

- take only by mouth. Doses may be taken as a single daily dose or in divided doses.

adults and children 12 years and over | take 1-3 softgels daily
children 2 to under 12 years of age | take 1 softgel daily
children under 2 years | ask a doctor

Other information

- each softgel contains: sodium 6 mg
- store at 25o C (77o F); excursions permitted between 15-30o C (59o- 86o F)

Inactive Ingredients

black iron oxide, D&C Red #33, FD&C blue #1, FD&C Red #40, FD&C Yellow #6, gelatin, glycerin, hypromellose, polyethylene glycol, propylene glycol, purified water, sorbitan, sorbitol, titanium dioxide

Questions or comments?

Call 1-877-753-3935 Monday-Friday 9AM-5PM EST

Principal Display Panel

COMPARE TO COLACE® REGULAR STRENGTH STOOL SOFTENER ACTIVE INGREDIENT**

Stool Softener

STOOL SOFTENER LAXATIVE

Docusate Sodium 100 mg

Stool Softener Laxative

Gentle & Effective,

Stimulant-free,

Relieves Constipation

SOFTGELS

**This product is not manufactured or distributed by Atlantis Consumer Healthcare Inc., distributor of Colace® Regular Strength Stool Softener.

TAMPER EVIDENT: DO NOT USE IF PRINTED SAFETY SEAL UNDER CAP IS BROKEN OR MISSING

DIST. BY MEIJER DISTRIBUTION, INC,

GRAND RAPIDS, MI 49544

Product Label

MEIJER Stool Softener